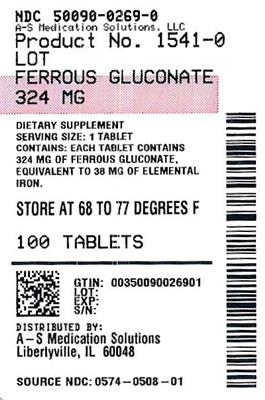 DRUG LABEL: Ferrous Gluconate
NDC: 50090-0269 | Form: TABLET
Manufacturer: A-S Medication Solutions
Category: other | Type: DIETARY SUPPLEMENT
Date: 20250106

ACTIVE INGREDIENTS: FERROUS GLUCONATE 38 mg/1 1
INACTIVE INGREDIENTS: SILICON DIOXIDE; ZEA MAYS (CORN) STARCH; TALC; POWDERED CELLULOSE; STEARIC ACID; CI 77891; POLYETHYLENE GLYCOL, UNSPECIFIED; SUCROSE; CALCIUM CARBONATE; MAGNESIUM STEARATE; VP/VA COPOLYMER; SHELLAC; COCOA BUTTER; BLUE 1; MALTODEXTRIN; LACTOFLAVIN; CARNAUBA WAX; WHITE WAX

Ferrous Gluconate Tablets

STATEMENT OF IDENTITY

Dietary Supplement

WARNING:

Accidental overdose of iron-containing products is a leading cause of fatal poisoning in children under 6. Keep this product out of reach of children. In case of accidental overdose, call a doctor or poison control center immediately.

WARNINGS:

Do not take within 2 hours of taking oral tetracycline antibiotics, since oral iron products tend to interfere with absorption of tetracycline. May cause gastrointestinal discomfort, nausea, constipation or diarrhea. If you are pregnant or nursing a baby, seek advice of a health professional before using this product. U.S. Consumer Product Safety Commission requires that iron-containing medicines and vitamins with iron be packaged in child-resistant closures. Parents should always properly resecure safety closures.

STORAGE:

Store at 20° to 25°C (68° to 77°F) [see USP Controlled Room Temperature]

Supplement Facts

Serving Size 1 Tablet
Amount Per Tablet | % Daily Value
Iron (as ferrous gluconate) 38 mg | 208%

Other ingredients: Colloidal Silicon Dioxide, Corn Starch, Talc, Powdered Cellulose, Sodium Starch Glycolate, Stearic Acid, Titanium Dioxide, Polyethylene Glycol, Sucrose, Calcium Carbonate, Magnesium Stearate, Copovidone, Shellac, Cocoa Butter, FD&C Blue No. 1 Aluminum Lake, Maltodextrin, Hypromellose, Riboflavin, Carnauba Wax, White Wax.

Distributed by Padagis®
Minneapolis, MN 55427

02-23